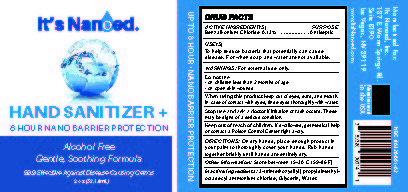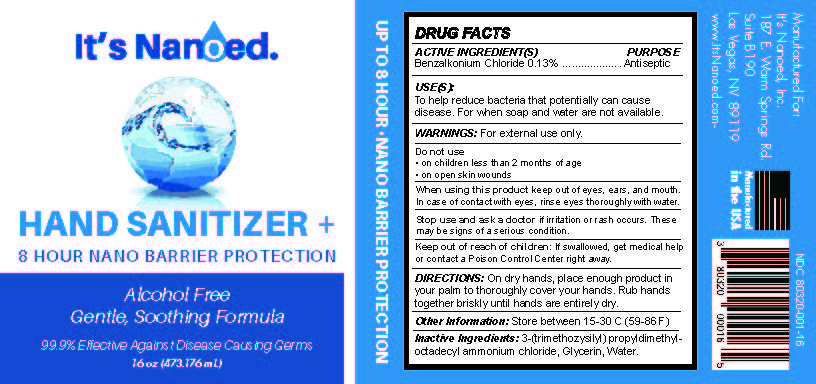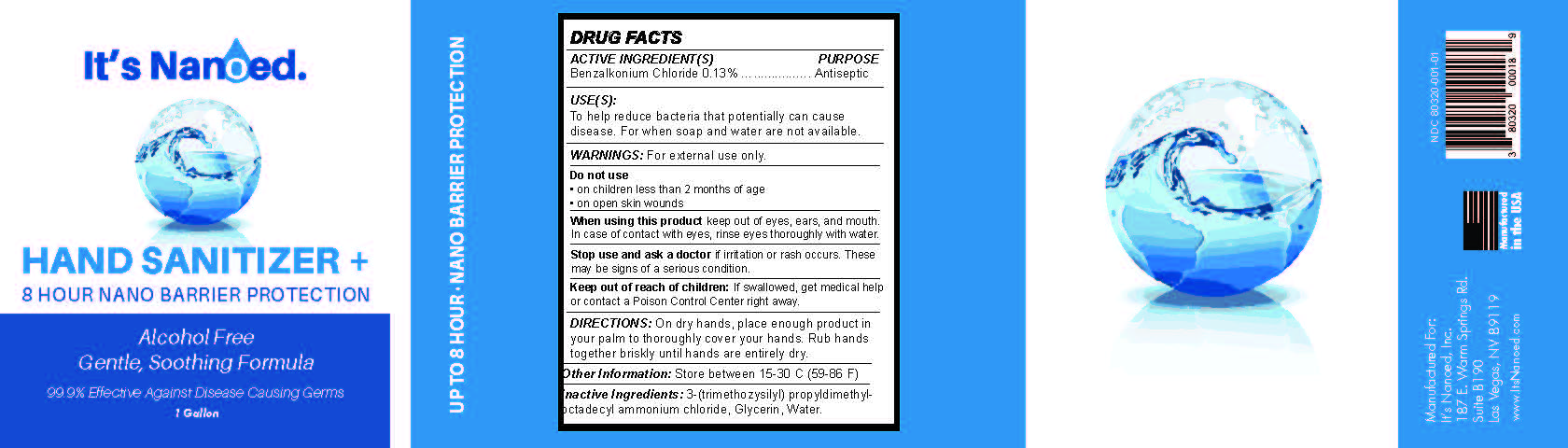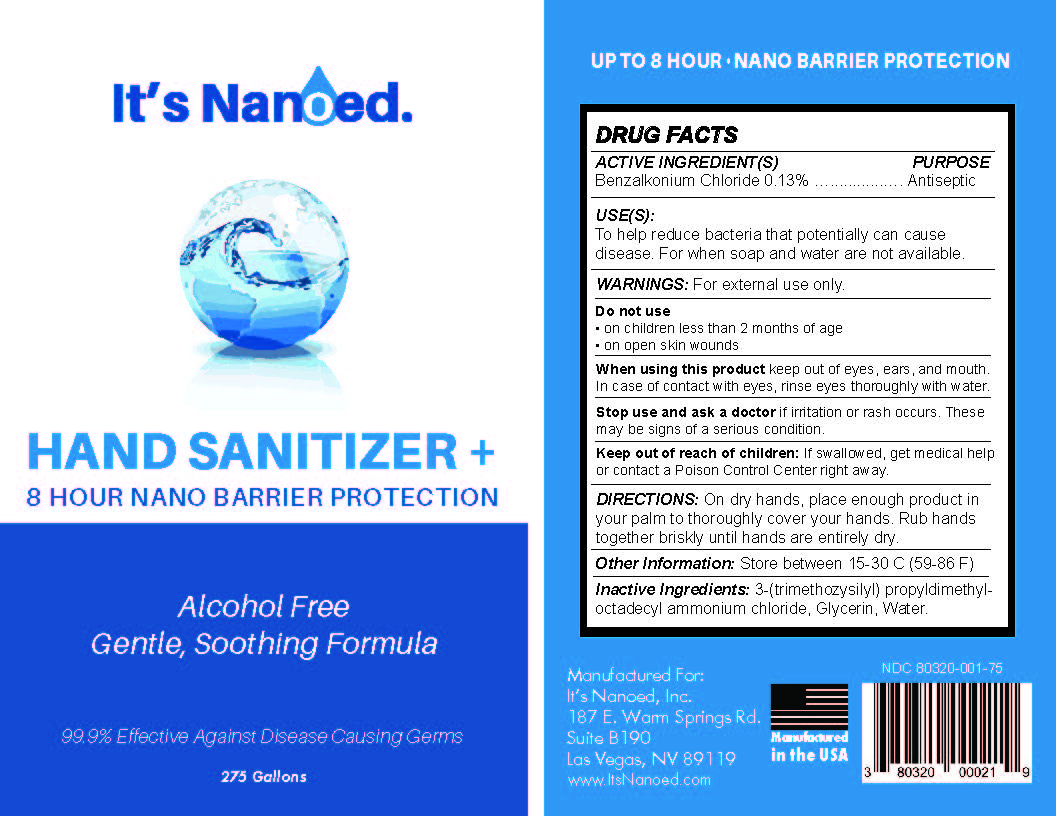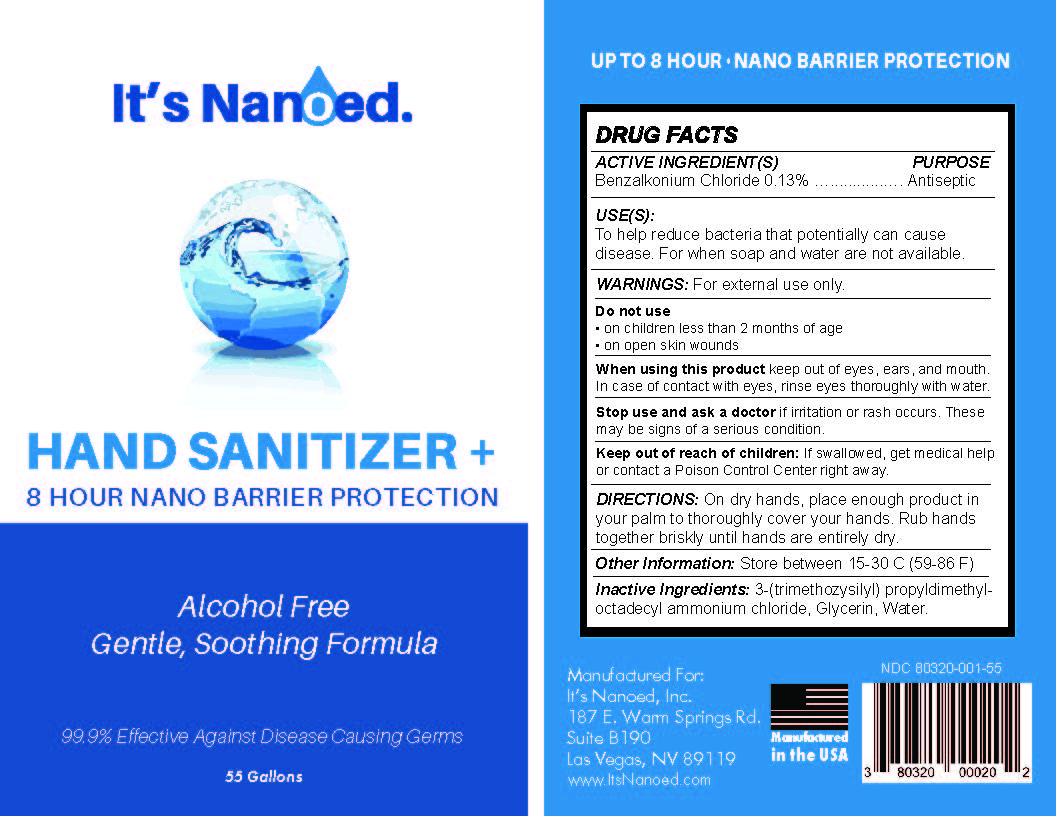 DRUG LABEL: Its Nanoed Hand
NDC: 80320-001 | Form: LIQUID
Manufacturer: It's Nanoed, Inc.
Category: otc | Type: HUMAN OTC DRUG LABEL
Date: 20210310

ACTIVE INGREDIENTS: BENZALKONIUM CHLORIDE 0.076 g/59 mL
INACTIVE INGREDIENTS: WATER; GLYCERIN; DIMETHYLOCTADECYL(3-(TRIMETHOXYSILYL)PROPYL)AMMONIUM CHLORIDE

It's Nanoed Hand Sanitizer +

Active Ingredient

Benzalkonium Chloride 0.13%

Purpose

Antiseptic

Uses

to help reduce bacteria that potentially can cause disease. For when soap and water are not available.

Warnings

For External Use only.

Do Not Use

On children less that 2 months of age

on open skin wounds

When using this product

keep out of eyes, ears, and mouth, in case of contact with eyes, rinse eyes thoroughly with water

Keep out of reach of children.

If swallowed, get medical help or contact a Poison Control Center right away

Directions

On dry hands, place enough product in your palm to thoroughly cover your hands. Rub hands together briskly until hands are entirely dry.

Other Information

Store between 15-30C (59-86F)

Inactive Ingredients

3-(trimethozysilyl) propyldimethyl-octadecyl ammonium chloride, Glycerin, water.